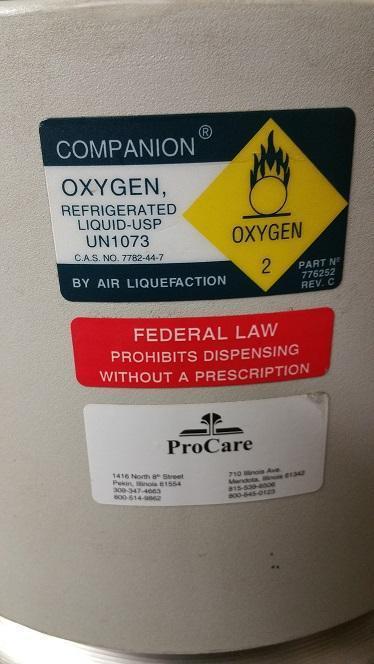 DRUG LABEL: Oxygen
NDC: 61210-001 | Form: GAS
Manufacturer: Pekin Prohealth Inc.
Category: prescription | Type: HUMAN PRESCRIPTION DRUG LABEL
Date: 20171205

ACTIVE INGREDIENTS: OXYGEN 990 mL/1 L

Oxygen

PACKAGE LABEL

COMPANION

OXYGEN, REFRIGERATED LIQUID-USP

UN1073

OXYGEN 2

BY AIR LIQUEFACTION

PART N2 776252 REV. C

FEDERAL LAW PROHIBITS DISPENSING WITHOUT A PRESCRIPTION

ProCare

1416 North 8th Street

Peking, Illinois 61554

309-347-4663

800-514-9862

710 Illinois Ave

Mandota, Illinois 61342

815-539-6506

800-645-0123